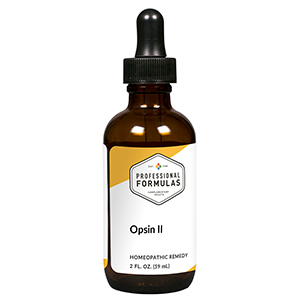 DRUG LABEL: Opsin II
NDC: 63083-6015 | Form: LIQUID
Manufacturer: Professional Complementary Health Formulas
Category: homeopathic | Type: HUMAN OTC DRUG LABEL
Date: 20190815

ACTIVE INGREDIENTS: ONION 3 [hp_X]/59 mL; AMBROSIA ARTEMISIIFOLIA WHOLE 3 [hp_X]/59 mL; EUPHRASIA STRICTA 3 [hp_X]/59 mL; WYETHIA HELENIOIDES ROOT 3 [hp_X]/59 mL; NAPHTHALENE 4 [hp_X]/59 mL; EPINEPHRINE 6 [hp_X]/59 mL; ARUNDO PLINIANA ROOT 6 [hp_X]/59 mL; SCHOENOCAULON OFFICINALE SEED 6 [hp_X]/59 mL; ARSENIC TRIOXIDE 12 [hp_X]/59 mL; HISTAMINE DIHYDROCHLORIDE 12 [hp_X]/59 mL; SODIUM CHLORIDE 12 [hp_X]/59 mL; TOBACCO LEAF 12 [hp_X]/59 mL
INACTIVE INGREDIENTS: ALCOHOL; WATER

X15

ACTIVE INGREDIENTS

Allium cepa 3X
Ambrosia artemisiaefolia 3X
Euphrasia officinalis 3X
Wyethia helenioides 3X
Naphthalinum 4X
Adrenalinum 6X
Arundo mauritanica 6X
Sabadilla 6X
Arsenicum album 12X
Histaminum hydrochloricum 12X
Natrum muriaticum 12X
Tabacum 12X

QUESTIONS

Professional Formulas

PO Box 2034 Lake Oswego, OR 97035

INDICATIONS

For the temporary relief of runny nose, sneezing, itching of the nose or throat, and itchy or watery eyes due to sensitivity to inhalant allergens.*

PURPOSE

*Claims based on traditional homeopathic practice, not accepted medical evidence. Not FDA evaluated.

WARNINGS

In case of overdose, get medical help or contact a poison control center right away.

Keep out of the reach of children.

PREGNANCY OR BREAST FEEDING

If pregnant or breastfeeding, ask a healthcare professional before use.

DIRECTIONS

Place drops under tongue 30 minutes before/after meals. Adults and children 12 years and over: Take 10 drops up to 3 times per day. Consult a physician for use in children under 12 years of age.

OTHER INFORMATION

Tamper resistant. If seal is broken, do not use. After opening, close container tightly and store at room temperature away from heat.

INACTIVE INGREDIENTS

20% ethanol, purified water.

LABEL

Est 1985

Professional Formulas

Complementary Health

Opsin II

Homeopathic Remedy

2 FL. OZ. (59 mL)